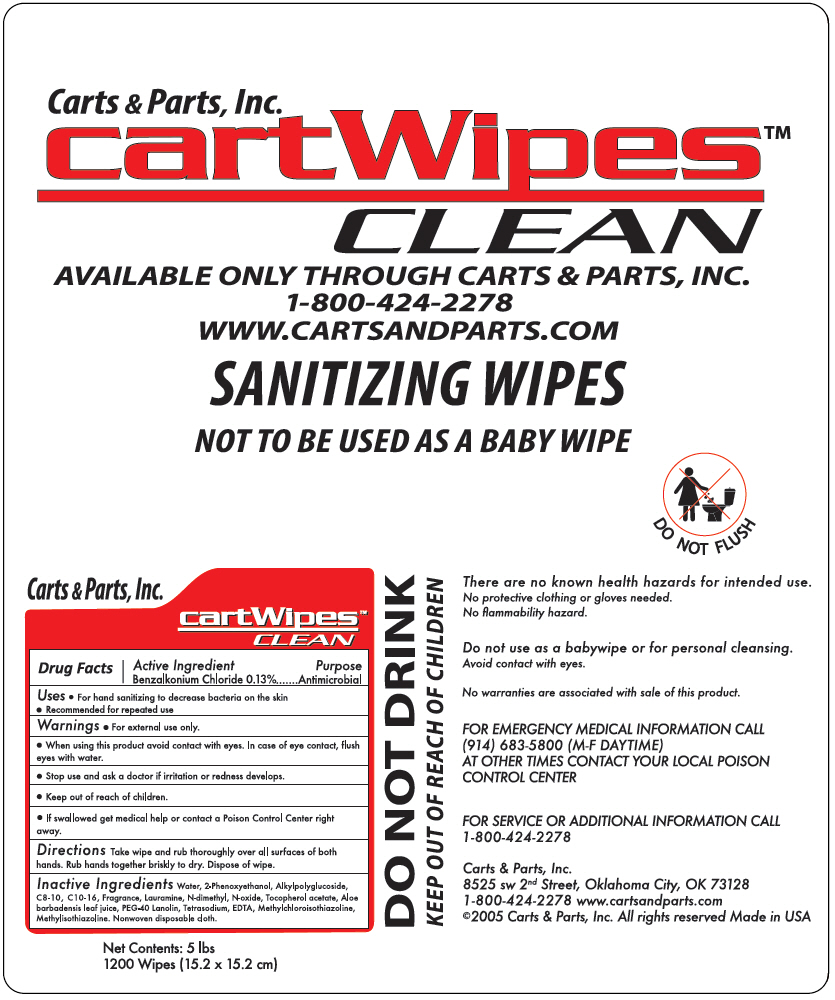 DRUG LABEL: Cart Wipes Clean Sanitizing Wipes
NDC: 82402-010 | Form: CLOTH
Manufacturer: Carts and Parts INC.
Category: otc | Type: HUMAN OTC DRUG LABEL
Date: 20250618

ACTIVE INGREDIENTS: BENZALKONIUM CHLORIDE 0.0019 g/1 1
INACTIVE INGREDIENTS: WATER; SODIUM LAURYLGLUCOSIDES HYDROXYPROPYLSULFONATE; LAURAMINE OXIDE; PHENOXYETHANOL; METHYLCHLOROISOTHIAZOLINONE/METHYLISOTHIAZOLINONE MIXTURE; EDETATE SODIUM; ALOE VERA LEAF; .ALPHA.-TOCOPHEROL ACETATE; PEG-75 LANOLIN

Cart Wipes™ Clean Sanitizing Wipes

Drug Facts

Active Ingredient

Benzalkonium Chloride 0.13%

Purpose

Antimicrobial

Uses

- For hand sanitizing to decrease bacteria on the skin
- Recommended for repeated use

Warnings

- For external use only.

- When using this product avoid contact with eyes. In case of eye contact, flush eyes with water.

- Stop use and ask a doctor if irritation or redness develops.

- Keep out of reach of children.
- If swallowed get medical help or contact a Poison Control Center right away.

Directions

Take wipe and rub thoroughly over all surfaces of both hands. Rub hands together briskly to dry. Dispose of wipe.

Inactive Ingredients

Water, 2-Phenoxyethanol, Alkylpolyglucoside, C8-10, C10-16, Fragrance, Lauramine, N-dimethyl, N-oxide, Tocopherol acetate, Aloe barbadensis leaf juice, PEG-40 Lanolin, Tetrasodium, EDTA, Methylchloroisothiazoline, Methylisothiazoline. Nonwoven disposable cloth.

QUESTIONS

FOR EMERGENCY MEDICAL INFORMATION CALL (914) 683-5800 (M-F DAYTIME)
AT OTHER TIMES CONTACT YOUR LOCAL POISON CONTROL CENTER

FOR SERVICE OR ADDITIONAL INFORMATION CALL 1-800-424-2278

PRINCIPAL DISPLAY PANEL - 1200 Wipe Pouch Label

Carts & Parts, Inc.

cartWipes™
CLEAN

AVAILABLE ONLY THROUGH CARTS & PARTS, INC.
1-800-424-2278
WWW.CARTSANDPARTS.COM

SANITIZING WIPES

NOT TO BE USED AS A BABY WIPE

DO NOT FLUSH